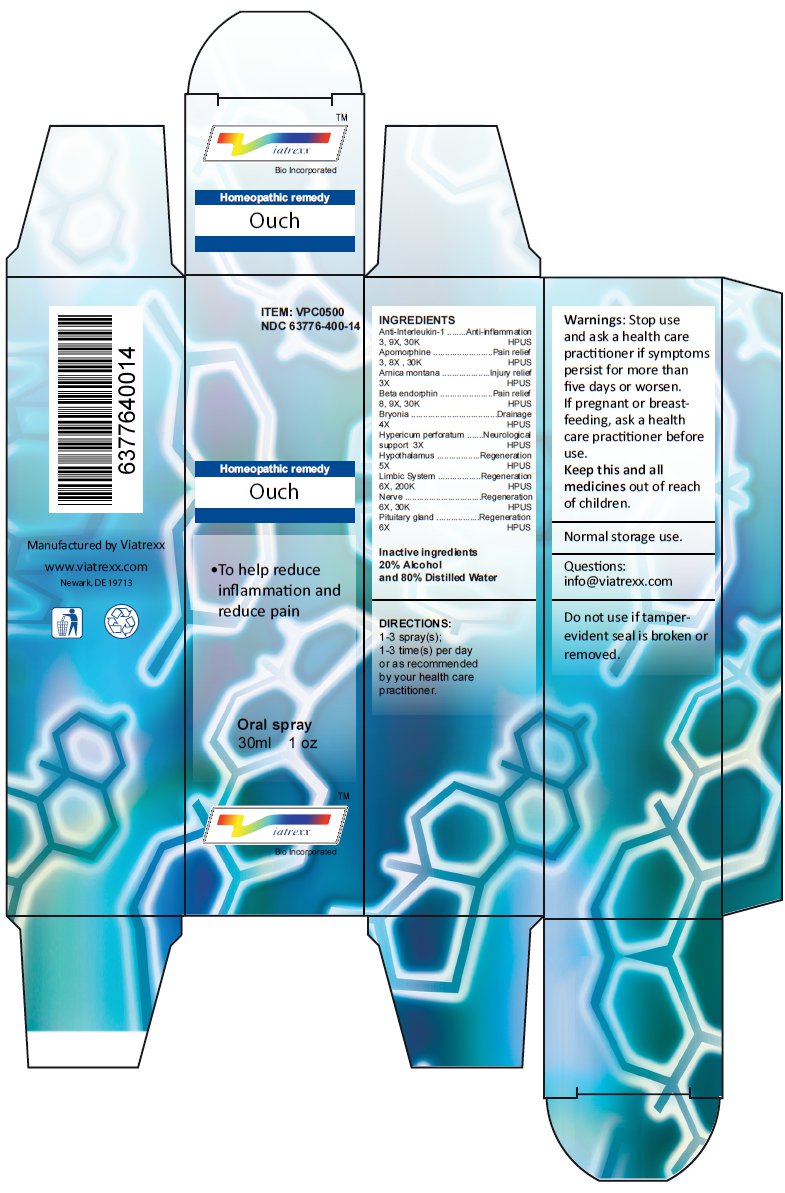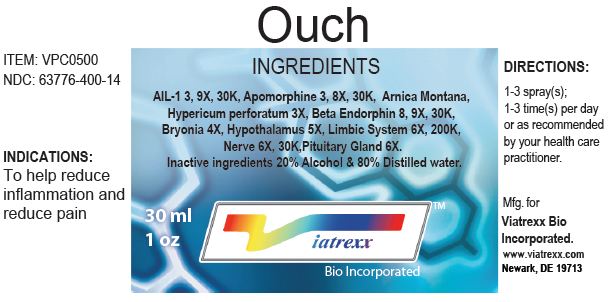 DRUG LABEL: Ouch 
NDC: 63776-400 | Form: SPRAY
Manufacturer: VIATREXX BIO INCORPORATED
Category: homeopathic | Type: HUMAN OTC DRUG LABEL
Date: 20120326

ACTIVE INGREDIENTS: Anti-interleukin-1.alpha. Immunoglobulin G Rabbit 9 [hp_X]/1 mL; Anti-interleukin-1.alpha. Immunoglobulin G Rabbit 30 {kp_C}/1 mL; Apomorphine 8 [hp_X]/1 mL; Apomorphine 30 {kp_C}/1 mL; Arnica Montana 3 [hp_X]/1 mL; Metenkefalin 9 [hp_X]/1 mL; Metenkefalin 30 {kp_C}/1 mL; Bryonia Alba Root 4 [hp_X]/1 mL; Hypericum Perforatum 3 [hp_X]/1 mL; Bos Taurus Hypothalamus 5 [hp_X]/1 mL; Sus Scrofa Hypothalamus 5 [hp_X]/1 mL; Bos Taurus Limbic System 6 [hp_X]/1 mL; Bos Taurus Limbic System 200 {kp_C}/1 mL; Sus Scrofa Limbic System 6 [hp_X]/1 mL; Sus Scrofa Limbic System 200 {kp_C}/1 mL; Bos Taurus Nerve 6 [hp_X]/1 mL; Bos Taurus Nerve 30 {kp_C}/1 mL; Sus Scrofa Nerve 6 [hp_X]/1 mL; Sus Scrofa Nerve 30 {kp_C}/1 mL; Bos Taurus Pituitary Gland 6 [hp_X]/1 mL; Sus Scrofa Pituitary Gland 6 [hp_X]/1 mL
INACTIVE INGREDIENTS: Water; Alcohol

Ouch

Active Ingredients

Anti-Interleukin-1 3 9X 30K, Apomorphine 3 8X 30K, Arnica montana 3X, Beta endorphin 8 9X 30K, Bryonia 4X, Hypericum perforatum 3X, Hypothalamus 5X, Limbic System 6X 200K, Nerve 6X 30K, Pituitary gland 6X

Purpose

Anti-Interleukin-1 | Anti-inflammation
Apomorphine | Pain relief
Arnica montana | Injury relief
Beta endorphin | Pain relief
Bryonia | Drainage
Hypericum perforatum | Neurological support
Hypothalamus | Regeneration
Limbic System | Regeneration
Nerve | Regeneration
Pituitary gland | Regeneration

Uses

To help reduce inflammation and reduce pain

Warnings

Stop use and ask a health care practitioner if symptoms persist for more than five days or worsen. If pregnant or breastfeeding, ask a health care practitioner before use.

KEEP OUT OF REACH OF CHILDREN

Keep this and all medicines out of reach of children.

Directions

1-3 spray(s); 1-3 time(s) per day or as recommended by your health care practitioner.

Other Ingredients

Alcohol and Distilled Water

Other Information

Normal storage use.
Do not use if tamper-evident seal is broken or removed.

Questions

info@viatrexx.com

Principal Display Panel

ITEM: VPC0500
NDC 63776-400-14
Homeopathic remedy
Ouch
• To help reduce inflammation and reduce pain
Oral spray
30ml 1 oz
Viatrexx™ Bio Incorporated
Manufactured by Viatrexx
www.viatrexx.com
Newark, DE 19713

Ouch
30 mL
1 oz
Viatrexx™ Bio Incorporated
ITEM: VPC0500
NDC: 63776-400-14
INDICATIONS:
To help reduce inflammation and reduce pain
DIRECTIONS:
1-3 spray(s); 1-3 time(s) per day or as recommended by your health care practitioner.
Mfg. for
Viatrexx Bio Incorporated.
www.viatrexx.com
Newark, DE 19713